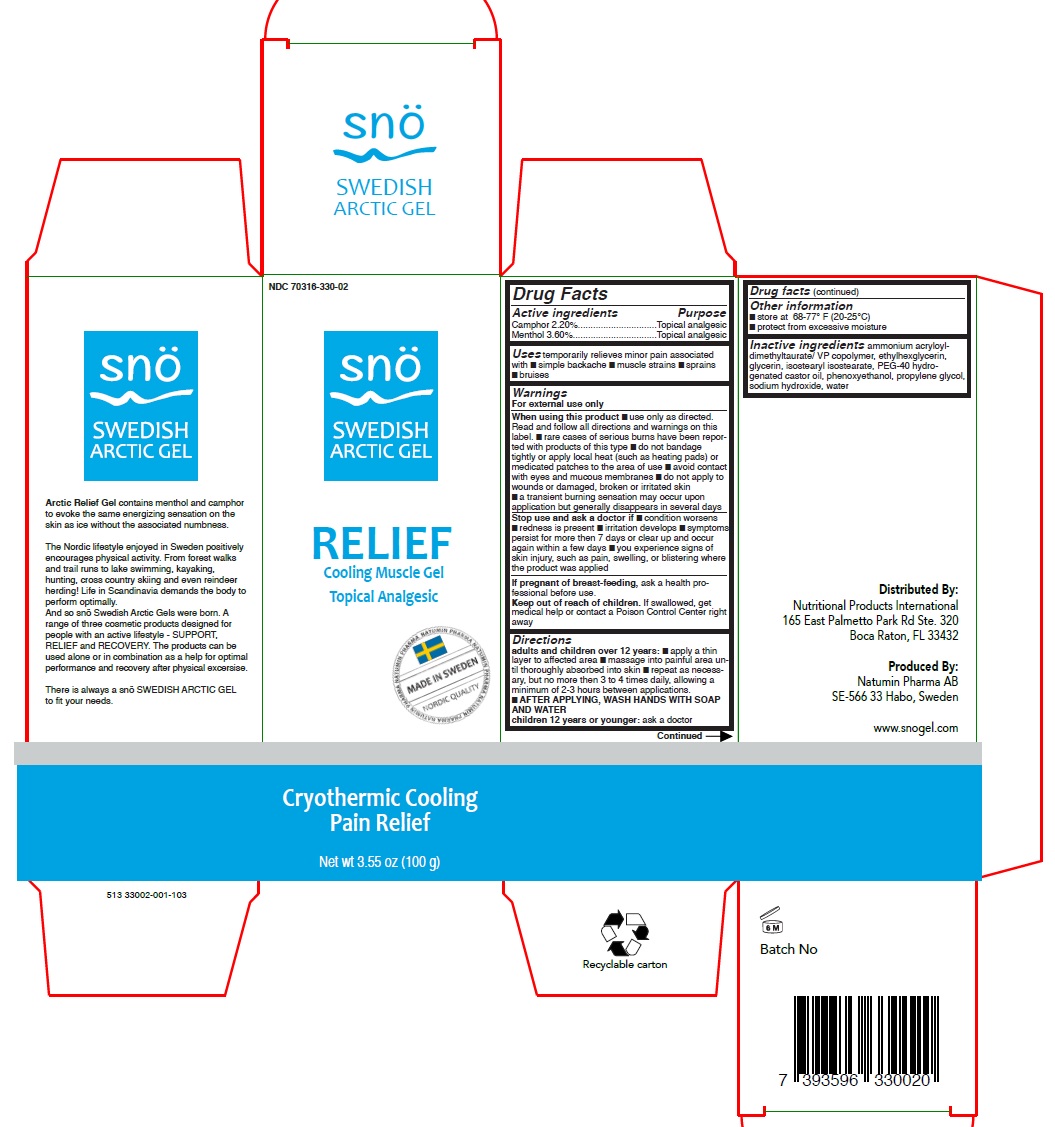 DRUG LABEL: Sno Swedish Arctic Gel Relief
NDC: 70316-330 | Form: GEL
Manufacturer: Natumin Pharma AB
Category: otc | Type: HUMAN OTC DRUG LABEL
Date: 20160105

ACTIVE INGREDIENTS: CAMPHOR (SYNTHETIC) 2.2 g/100 g; MENTHOL, UNSPECIFIED FORM 3.6 g/100 g
INACTIVE INGREDIENTS: WATER; AMMONIUM ACRYLOYLDIMETHYLTAURATE/VP COPOLYMER; ETHYLHEXYLGLYCERIN; ISOSTEARYL ISOSTEARATE; POLYOXYL 40 HYDROGENATED CASTOR OIL; PHENOXYETHANOL; PROPYLENE GLYCOL; SODIUM HYDROXIDE

Active Ingredients

Camphor 2.2%

Menthol 3.6%

Purpose

Topical Analgesic

Uses

temporarily relieves minor pain associated with

- simple backache
- muscle strains
- sprains
- bruises

Warning

For external use only

When using this product

- use only as directed
- read and follow all directions and warnings on this label
- rare cases of serious burns have been reported with products of this type
- do not bandage tightly or apply local heat (such as heating pads) or medicated patches to the area of use
- avoid contact with eyes and mucous membranes
- do not apply to wounds or damaged, broken, or irritated skin
- a transient burning sensation may occur upon application but generally disappears in several days

Stop use and ask doctor if

- Condition worsens
- redness is present
- irritation develops
- symptoms persis for more than 7 days or clear up and occur again within a few days
- you experience signs of skin injury, such as pain, swelling, or blistering where the product was applied

If pregnant or breast feeding

ask a health professional before use

Keep out of reach of children

If swallowed, get medical help or contact a Poison Control Center right away

Directions

adults and children over 12 years:

apply a thin layer to affected area

massage into painful area until thoroughly absorbed into skin

repeat as necessary, but no more than 3 to 4 times daily, allowing a minimum of 2-3 hours between applications.

After applying, wash hands with soap and water.

Children 12 years or younger: ask a doctor

Other Information

Store at 68-77°F (20-25°C)

Protect from excessive moisture

Inactive Ingredients

ammonium acryloyldimethyltaurate/ VP copolymer

ethylhexylglycerin

glycerin

isostearyl isostearate

PEG-40 hydrogenated castor oil

phenoxyethanol

propylene glycol

sodium hydroxide

water